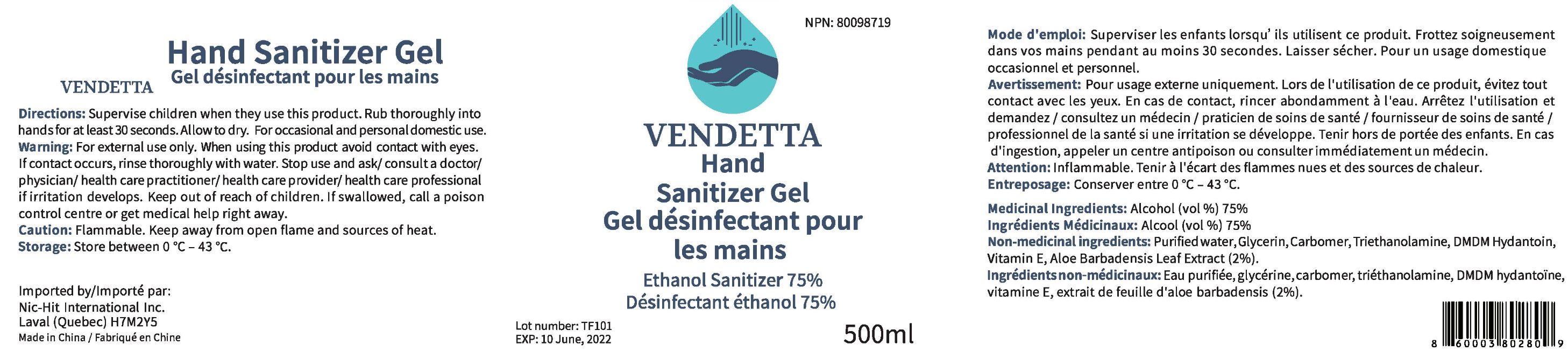 DRUG LABEL: Vendetta Hand Sanitizer
NDC: 80355-001 | Form: GEL
Manufacturer: Nic-Hit International Inc.
Category: otc | Type: HUMAN OTC DRUG LABEL
Date: 20200831

ACTIVE INGREDIENTS: ALCOHOL 375 mL/500 mL
INACTIVE INGREDIENTS: DMDM HYDANTOIN 1 mL/500 mL; GLYCERIN 0.5 mL/500 mL; ALOE ANDONGENSIS LEAF 10 mL/500 mL; CARBOMER 940 1.25 mL/500 mL; TROLAMINE 1.25 mL/500 mL; WATER 106 mL/500 mL; ALPHA-TOCOPHEROL 5 mL/500 mL

ACTIVE INGREDIENT

Alcohol 75 % v/v. Purpose: Antiseptic

PURPOSE

Antiseptic.

WARNINGS

Keep away from Children.

Keep out of direct sunlight.

DO NOT SWALLOW.

INACTIVE INGREDIENT

Water, Glycerin, Carbomer, Triethanolamine, DMD Hydantoin, Vitamin E, Aloe Barbadensis leaf extract

PACKAGE LABEL

500 mL NDC: 80355-001-01